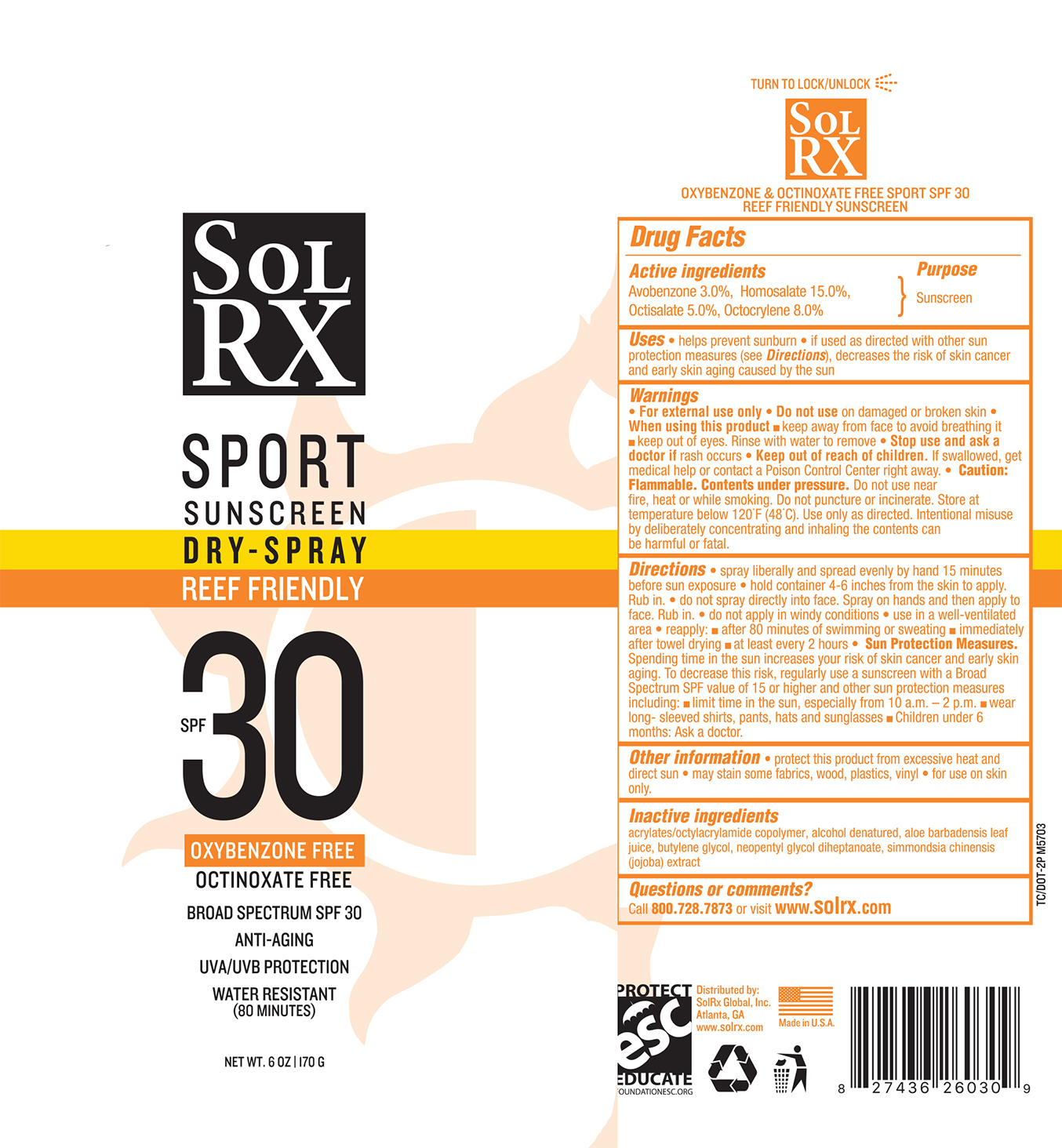 DRUG LABEL: SolRX Sport SPF 30 C-Spray
NDC: 73440-6030 | Form: AEROSOL, SPRAY
Manufacturer: Cross Brands Contract Filling
Category: otc | Type: HUMAN OTC DRUG LABEL
Date: 20210219

ACTIVE INGREDIENTS: OCTOCRYLENE 13.6 g/170 g; AVOBENZONE 5.1 g/170 g; HOMOSALATE 25.5 g/170 g; OCTISALATE 8.5 g/170 g
INACTIVE INGREDIENTS: ALCOHOL 104.6 g/170 g

Sol RX Sport SPF 30 C-Spray